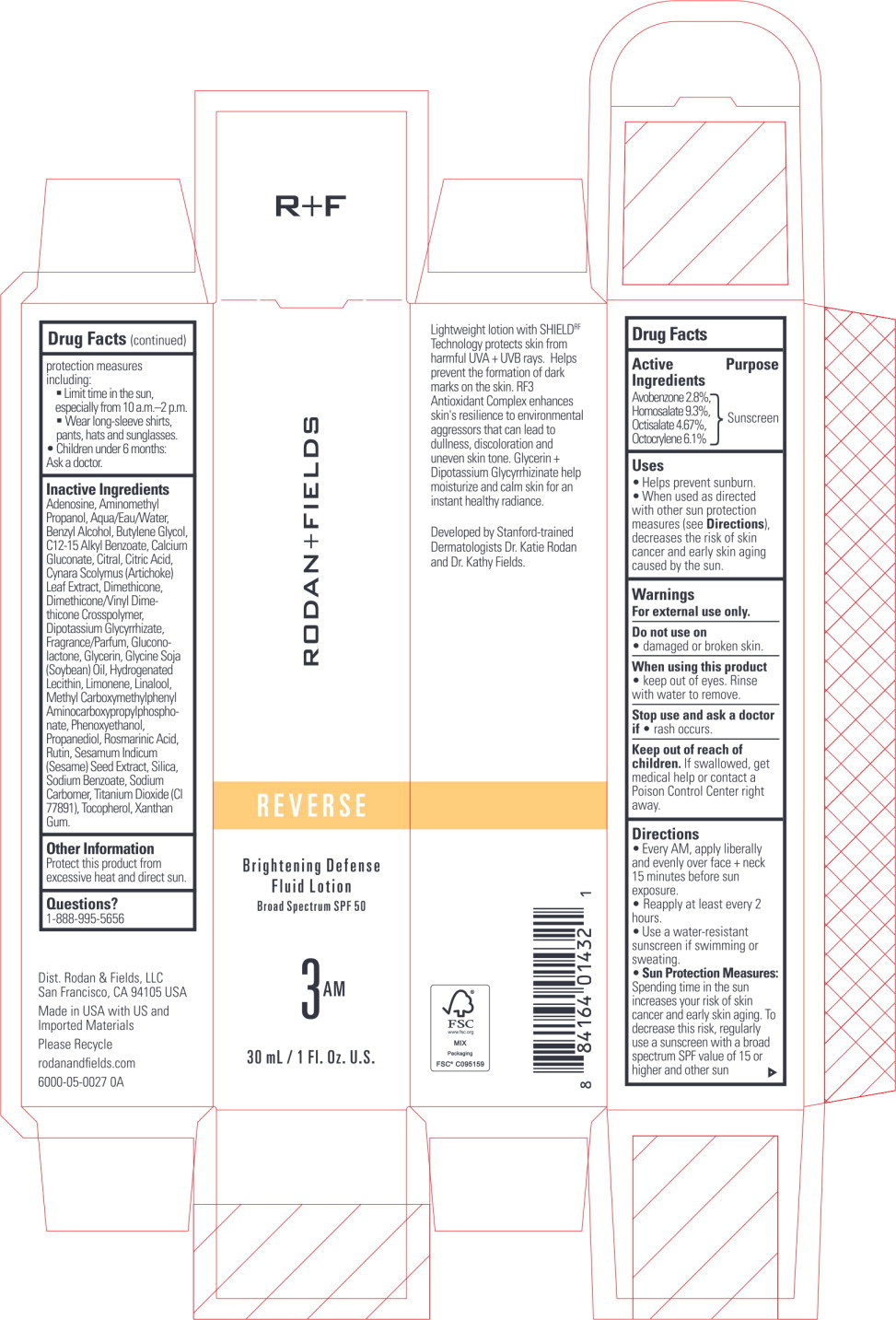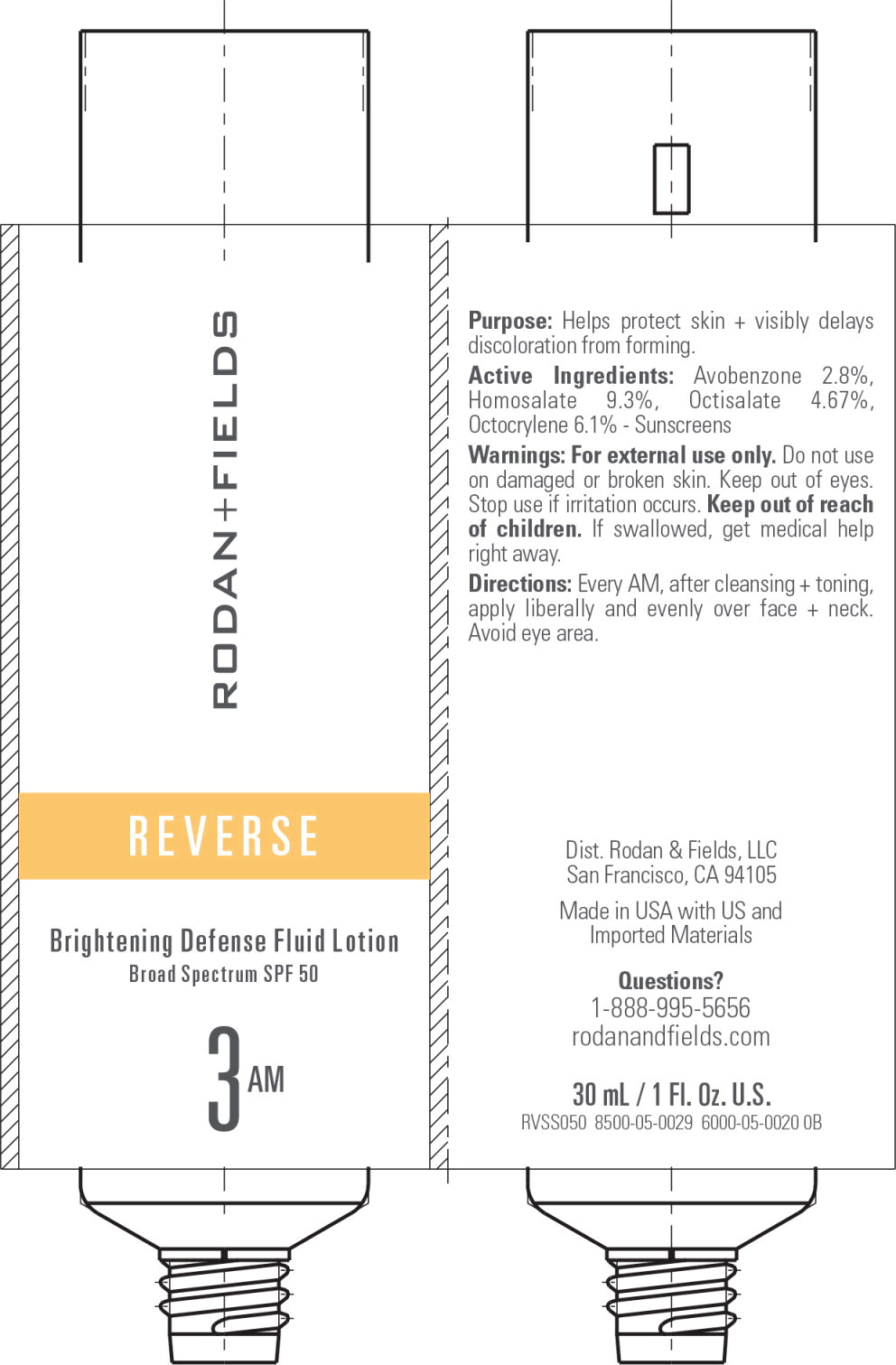 DRUG LABEL: REVERSE Brightening Defense Fluid
NDC: 14222-2300 | Form: LOTION
Manufacturer: Rodan & Fields
Category: otc | Type: HUMAN OTC DRUG LABEL
Date: 20251215

ACTIVE INGREDIENTS: AVOBENZONE 0.028 g/1 mL; HOMOSALATE 0.093 g/1 mL; OCTOCRYLENE 0.061 g/1 mL; OCTISALATE 0.0467 g/1 mL
INACTIVE INGREDIENTS: ADENOSINE; AMINOMETHYLPROPANOL; BENZYL ALCOHOL; BUTYLENE GLYCOL; ALKYL (C12-15) BENZOATE; CALCIUM GLUCONATE; CARBOXYPOLYMETHYLENE; CITRAL; CITRIC ACID MONOHYDRATE; CYNARA SCOLYMUS LEAF; DIMETHICONE; DIMETHICONE/VINYL DIMETHICONE CROSSPOLYMER (SOFT PARTICLE); GLYCYRRHIZINATE DIPOTASSIUM; GLUCONOLACTONE; GLYCERIN; HYDROGENATED SOYBEAN LECITHIN; LIMONENE, (+)-; LINALOOL, (+/-)-; PHENOXYETHANOL; PROPANEDIOL; ROSMARINIC ACID; RUTIN; SESAME SEED; SILICON DIOXIDE; SODIUM BENZOATE; SOYBEAN OIL; TITANIUM DIOXIDE; TOCOPHEROL; WATER; XANTHAN GUM

Drug Facts

Active Ingredients

Avobenzone 2.8%,

Homosalate 9.3%,

Octisalate 4.67%,

Octocrylene 6.1%

Purpose

Sunscreen

Uses

- Helps prevent sunburn.
- When used as directed with other sun protection measures (see Directions), decreases the risk of skin cancer and early skin aging caused by the sun.

Warnings

For external use only.

Do not use on

- damaged or broken skin.

When using this product

- keep out of eyes. Rinse with water to remove.

Stop use and ask a doctor if

- rash occurs.

Keep out of reach of children. If swallowed, get medical help or contact a Poison Control Center right away.

Directions

- Every AM, apply liberally and evenly over face + neck 15 minutes before sun exposure.
- Reapply at least every 2 hours.
- Use a water-resistant sunscreen if swimming or sweating.
- Sun Protection Measures: Spending time in the sun increases your risk of skin cancer and early skin aging. To decrease this risk, regularly use a sunscreen with a broad spectrum SPF value of 15 or higher and other sun

protection measures including:

- Limit time in the sun, especially from 10 a.m-2 p.m.
- Wear long-sleeve shirts, pants, hats and sunglasses.
- Children under 6 months: Ask a doctor.

Inactive Ingredients

Adenosine, Aminomethyl Propanol, Aqua/Eau/Water, Benzyl Alcohol, Butylene Glycol, C12-15 Alkyl Benzoate, Calcium Gluconate, Citral, Citric Acid, Cynara Scolymus (Artichoke) Leaf Extract, Dimethicone, Dimethicone/Vinyl Dimethicone Crosspolymer, Dipotassium Glycyrrhizate, Fragrance/Parfum, Gluconolactone, Glycerin, Glycine Soja (Soybean) Oil, Hydrogenated Lecithin, Limonene, Linalool, Methyl Carboxymethylphenyl Aminocarboxypropylphosphonate, Phenoxyethanol, Propanediol, Rosmarinic Acid, Rutin, Sesamum Indicum (Sesame) Seed Extract, Silica, Sodium Benzoate, Sodium Carbomer, Titanium Dioxide (Cl 77891), Tocopherol, Xanthan Gum.

Other Information

Protect this product from excessive heat and direct sun.

Questions?

1-888-995-5656

Principal Display Panel - 30 mL Carton Label

RODAN+FIELDS

REVERSE

Brightening Defense
Fluid Lotion

Broad Spectrum SPF 50

3AM

30 mL/1. Fl. Oz. U.S.

Principal Display Panel - 30 mL Tube Label

RODAN+FIELDS

REVERSE

Brightening Defense Fluid Lotion

Broad Spectrum SPF 50

3AM